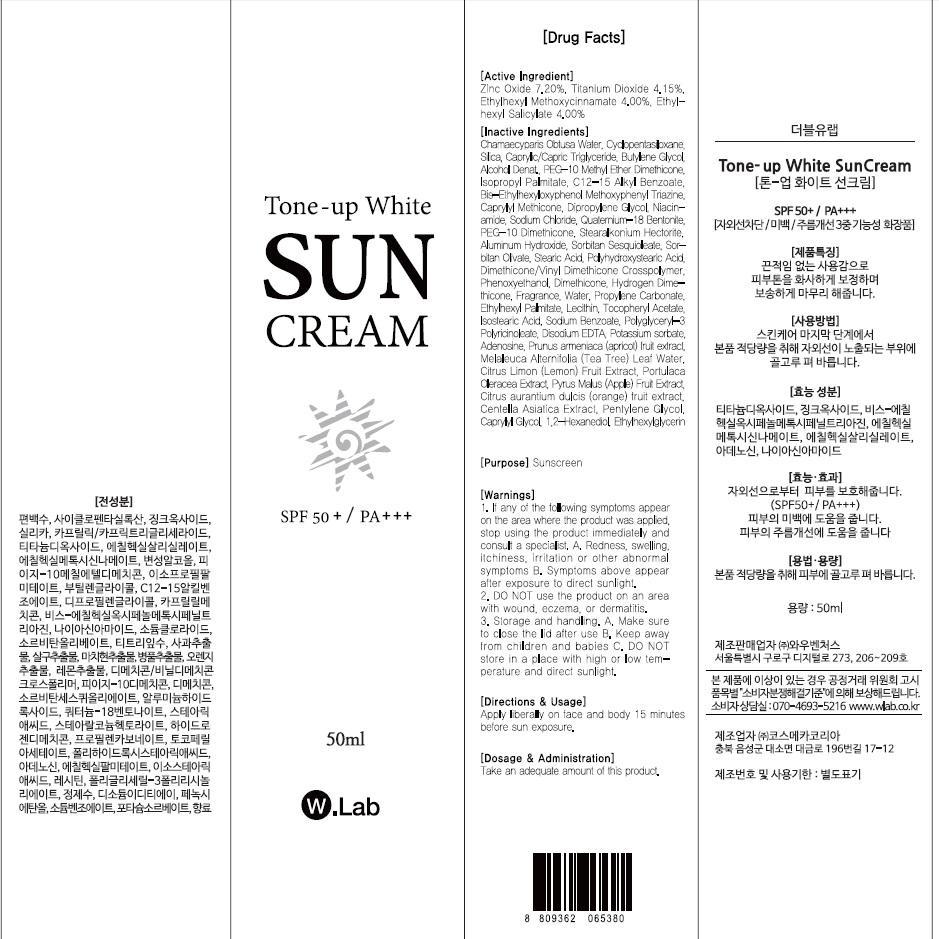 DRUG LABEL: TONE UP WHITE SUN
NDC: 69894-310 | Form: CREAM
Manufacturer: WOW VENTURES
Category: otc | Type: HUMAN OTC DRUG LABEL
Date: 20150626

ACTIVE INGREDIENTS: Zinc Oxide 3.60 mg/50 mL; Titanium Dioxide 2.07 mg/50 mL; Octinoxate 2.00 mg/50 mL; Octisalate 2.00 mg/50 mL
INACTIVE INGREDIENTS: Butylene Glycol

ACTIVE INGREDIENT

Active Ingredient: Zinc Oxide 7.20%, Titanium Dioxide 4.15%, Ethylhexyl Methoxycinnamate 4.00%, Ethylhexyl Salicylate 4.00%

INACTIVE INGREDIENT

Inactive Ingredients: Chamaecyparis Obtusa Water, Cyclopentasiloxane, Silica, Caprylic/Capric Triglyceride, Butylene Glycol, Alcohol Denat., PEG-10 Methyl Ether Dimethicone, Isopropyl Palmitate, C12-15 Alkyl Benzoate, Bis-Ethylhexyloxyphenol Methoxyphenyl Triazine, Caprylyl Methicone, Dipropylene Glycol, Niacinamide, Sodium Chloride, Quaternium-18 Bentonite, PEG-10 Dimethicone, Stearalkonium Hectorite, Aluminum Hydroxide, Sorbitan Sesquioleate, Sorbitan Olivate, Stearic Acid, Polyhydroxystearic Acid, Dimethicone/Vinyl Dimethicone Crosspolymer, Phenoxyethanol, Dimethicone, Hydrogen Dimethicone, Fragrance, Water, Propylene Carbonate, Ethylhexyl Palmitate, Lecithin, Tocopheryl Acetate, Isostearic Acid, Sodium Benzoate, Polyglyceryl-3 Polyricinoleate, Disodium EDTA, Potassium sorbate, Adenosine, Prunus armeniaca (apricot) fruit extract, Melaleuca Alternifolia (Tea Tree) Leaf Water, Citrus Limon (Lemon) Fruit Extract, Portulaca Oleracea Extract, Pyrus Malus (Apple) Fruit Extract, Citrus aurantium dulcis (orange) fruit extract, Centella Asiatica Extract, Pentylene Glycol, Caprylyl Glycol, 1,2-Hexanediol, Ethylhexylglycerin

PURPOSE

Purpose: Sunscreen

WARNINGS

Warnings: 1. If any of the following symptoms appear on the area where the product was applied, stop using the product immediately and consult a specialist. A. Redness, swelling, itchiness, irritation or other abnormal symptoms B. Symptoms above appear after exposure to direct sunlight 2. Do NOT use the product on an area with wound, eczema, or dermatitis 3. Storage and handling. A. Make sure to close the lid after use B. Keep away from children and babies C. Do NOT store in a place with high or low temperature and direct sunlight

DESCRIPTION

Directions & Usage: Apply liberally on face and body 15 minutes before sun exposure.

Dosage & Administration: Take an adequate amount of this product.